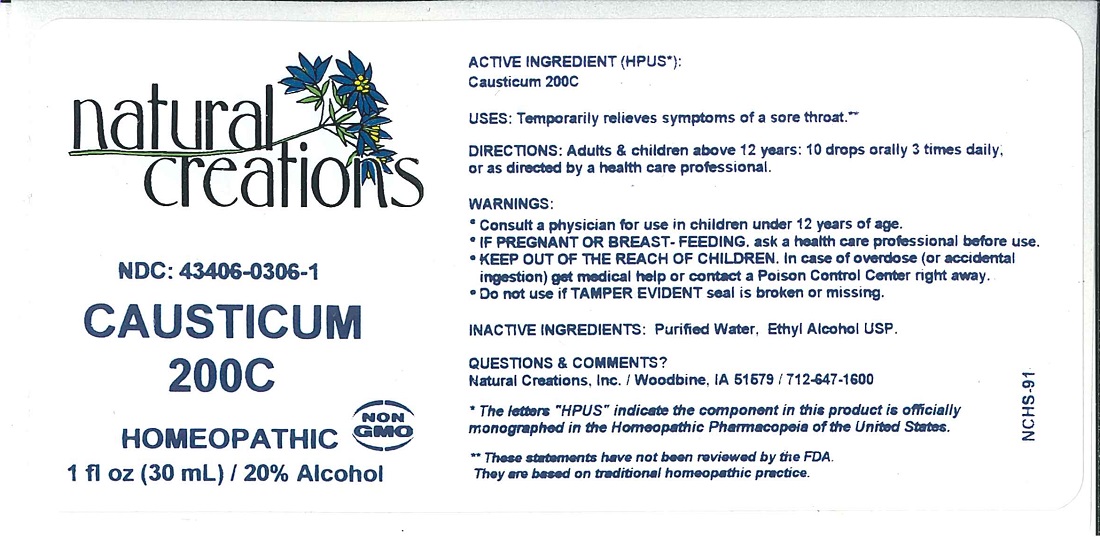 DRUG LABEL: Causticum 200C
NDC: 43406-0306 | Form: LIQUID
Manufacturer: Natural Creations, Inc
Category: homeopathic | Type: HUMAN OTC DRUG LABEL
Date: 20221219

ACTIVE INGREDIENTS: CAUSTICUM 200 [hp_C]/1 mL
INACTIVE INGREDIENTS: WATER; ALCOHOL

CAUSTICUM 200C

ACTIVE INGREDIENT (HPUS*): Causticum 200C

INDICATIONS AND USAGE

USES: Temporarily relieves symptoms of a sore throat.**

PURPOSE

USES: Temporarily relieves symptoms of a sore throat.**

DOSAGE AND ADMINISTRATION

DIRECTIONS: Adults & children above 12 years: 10 drops orally 3 times daily, or as directed by a health care professional.

KEEP OUT OF REACH OF CHILDREN

KEEP OUT OF THE REACH OF CHILDREN. In case of overdose (or accidental ingestion) get medical help or contact a Poison Control Center right away.

WARNINGS:

- Consult a physician for use in children under 12 years of age.
- IF PREGNANT OR BREAST-FEEDING, ask a health care professional before use.
- KEEP OUT OF THE REACH OF CHILDREN. In case of overdose (or accidental ingestion) get medical help or contact a Poison Control Center right away.
- Do not use if TAMPER EVIDENT seal is broken or missing.

INACTIVE INGREDIENTS: Purified Water, Ethyl Alcohol USP.

QUESTIONS & COMMENTS?

Natural Creations, Inc. / Woodbine, IA 51579 / 712-647-1600

REFERENCES

*The letters "HPUS" indicate the component in this product is officially monographed in the Homeopathic Pharmacopeia of the United States.

**Claims based on traditional homeopathic practice, not accepted medical evidence. Not FDA evaluated.

PACKAGE LABEL

NDC: 43406-0306-1

CAUSTICUM 200C

homeopathic

1 fl oz (30 mL) / 20% Alcohol